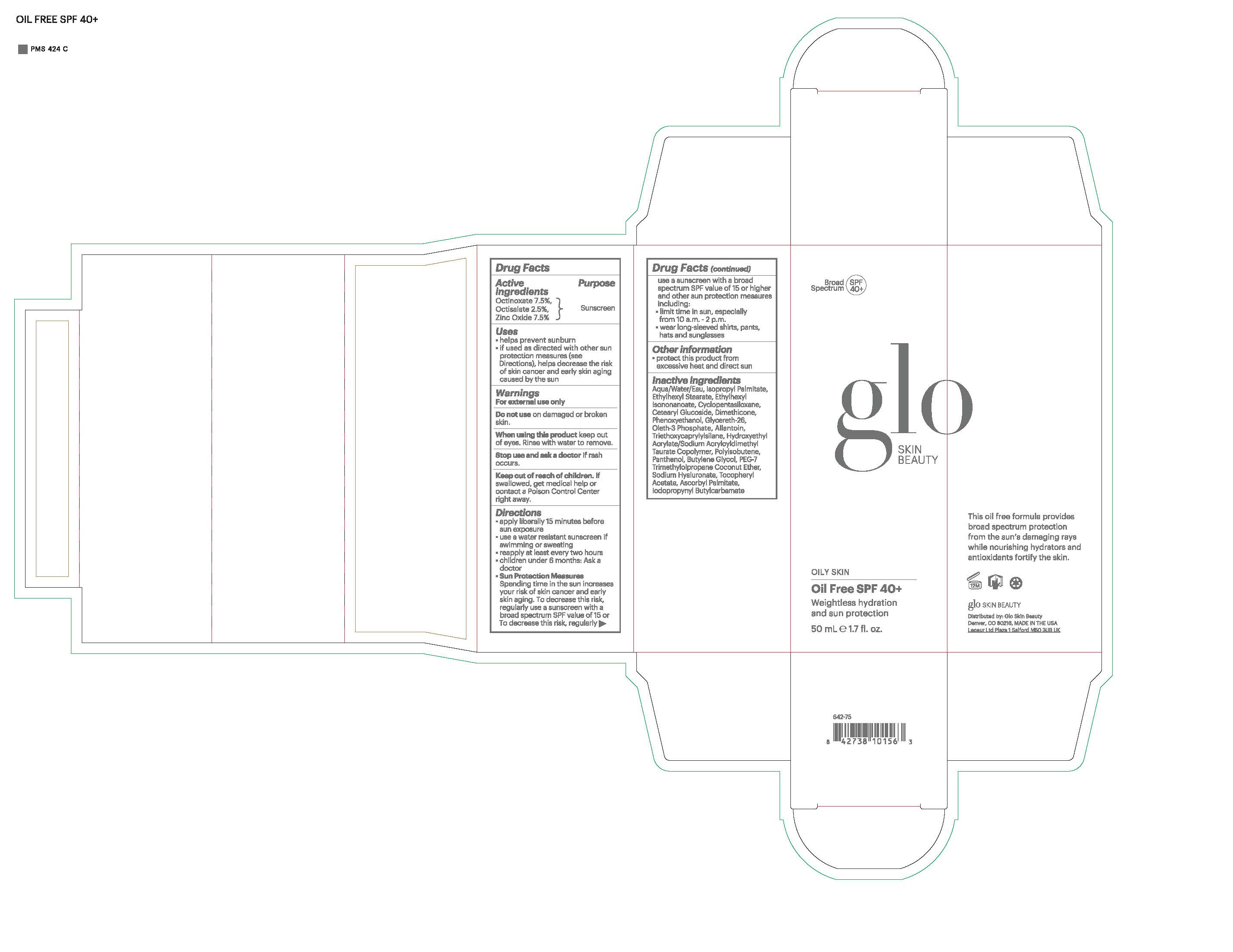 DRUG LABEL: glo SKIN BEAUTY Oil Free SPF 40
NDC: 60541-1000 | Form: LOTION
Manufacturer: Hayden Caleel LLC
Category: otc | Type: HUMAN OTC DRUG LABEL
Date: 20250105

ACTIVE INGREDIENTS: OCTINOXATE 7.5 g/100 g; OCTISALATE 2.5 g/100 g; ZINC OXIDE 7.5 g/100 g
INACTIVE INGREDIENTS: WATER; ISOPROPYL PALMITATE; ETHYLHEXYL STEARATE; ETHYLHEXYL ISONONANOATE; CETEARYL GLUCOSIDE; DIMETHICONE; PHENOXYETHANOL; GLYCERETH-26; OLETH-3 PHOSPHATE; ALLANTOIN; TRIETHOXYCAPRYLYLSILANE; BUTYLENE GLYCOL; PANTHENOL; ASCORBYL PALMITATE; IODOPROPYNYL BUTYLCARBAMATE

DRUG FACTS

Active Ingredients

Octinoxate 7.5%

Octisalate 2.5%

Zinc Oxie 7.5%

Uses

• helps prevent sunburn • if used as directed with other
sun protection measures (see Directions), decreases the
risk of skin cancer and early skin aging caused by the sun

Warnings

For external use only
Do not use on damaged or broken skin
When using this product keep out of eyes. Rinse with water to remove.
Stop use and ask a docor if rash occurs
Keep out of reach of children. If swalled, get medical help or contact a Poison Control Center right away.

Directions

• apply generously 15 minutes before sun exposure
• reapply at least every 2 hours
• use a water-resistant sunscreen if swimming or sweating
• Sun Protection Measures. Spending time in the sun
increases your risk of skin cancer and early skin aging. To decrease
this risk, regularly use a sunscreen with a Broad Spectrum SPF
value of 15 or higher and other sun protection measures including:
• limit time in the sun, especially from 10 a.m. - 2 p.m.
• wear long-sleeved shirts, pants, hats, and sunglasses
• children under 6 months of age: Ask a doctor

Inactive ingredients

Aqua/Water/Eau, Isopropyl Palmitate, Ethylhexyl Stearate, Ethylhexyl Isononanoate, Cyclopentasiloxane, Cetearyl Glucoside, Dimethicone, Phenoxyethanol, Glycereth-26, Oleth-3 Phosphate, Allantoin, Triethoxycaprylylsilane, Hydroxyethyl Acrylate/Sodium Acryloyldimethyl Taurate Copolymer, Polyisobutene, Panthenol, Butylene Glycol, PEG-7 Trimethylolpropane Coconut Ether, Sodium Hyaluronate, Tocopheryl Acetate, Ascorbyl Palmitate, Iodopropynyl Butylcarbamate

Other Information

• protect the product in this container from excessive
heat and direct sun

Keep out of reach of children

Purpose

Sunscreen